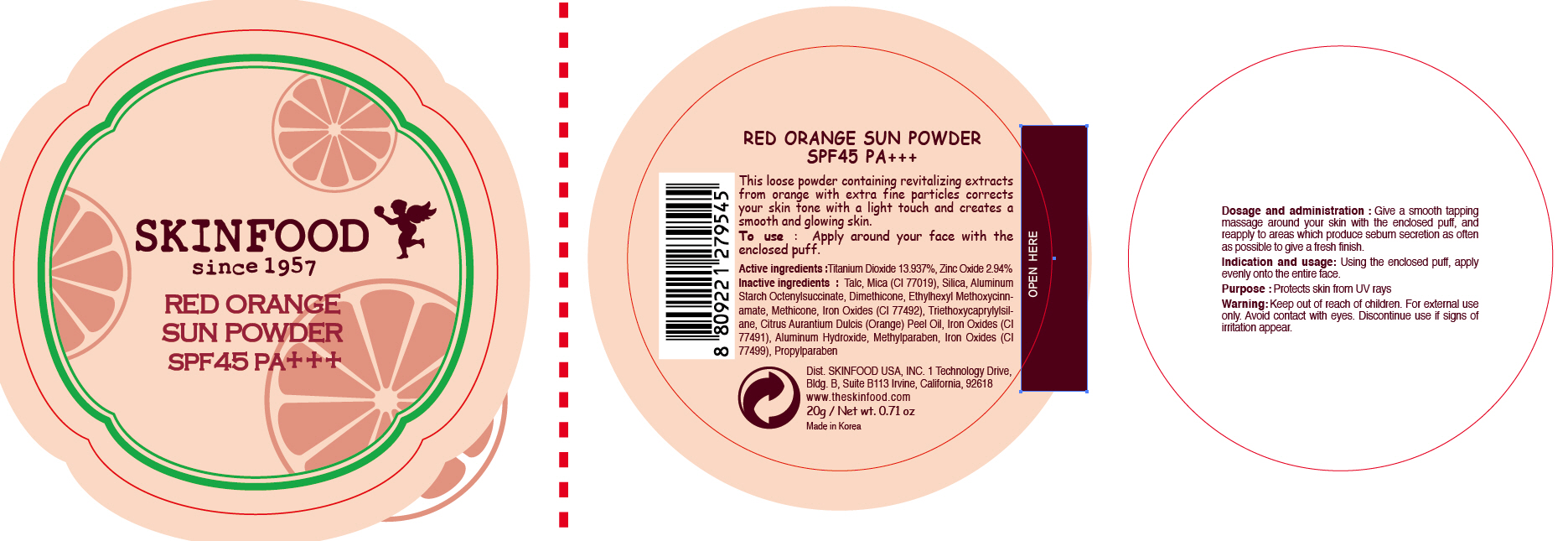 DRUG LABEL: RED ORANGE SUN
NDC: 76214-038 | Form: POWDER
Manufacturer: SKINFOOD CO., LTD.
Category: otc | Type: HUMAN OTC DRUG LABEL
Date: 20111009

ACTIVE INGREDIENTS: TITANIUM DIOXIDE 2.79 g/20 g; ZINC OXIDE 0.59 g/20 g
INACTIVE INGREDIENTS: TALC; MICA; SILICON DIOXIDE; ALUMINUM STARCH OCTENYLSUCCINATE; DIMETHICONE; OCTINOXATE; TRIETHOXYCAPRYLYLSILANE; ORANGE; ALUMINUM HYDROXIDE; METHYLPARABEN; PROPYLPARABEN

Drug Facts

ACTIVE INGREDIENT

Active ingredients: TITANIUM DIOXIDE 13.937%, ZINC OXIDE 2.94%

Inactive ingredients:
Talc, Mica (CI 77019), Silica, Aluminum Starch Octenylsuccinate, Dimethicone, Ethylhexyl Methoxycinnamate, Methicone, Iron Oxides (CI 77492), Triethoxycaprylylsilane, Citrus Aurantium Dulcis (Orange) Peel Oil, Iron Oxides (CI 77491), Aluminum Hydroxide, Methylparaben, Iron Oxides (CI 77499), Propylparaben

Purpose: Protects skin from UV rays.

Warnings:
For external use only.
Avoid contact with eyes.
Discontinue use if signs of irritation appear.

Keep out of reach of children:
Keep out of reach of children.

INDICATIONS AND USAGE

Indication and usage: Using the enclosed puff, apply evenly onto the entire face.

Dosage and administration:
Give a smooth tapping massage around your skin with the enclosed puff, and reapply to areas which produce sebum secretion as often as possible to give a fresh finish.